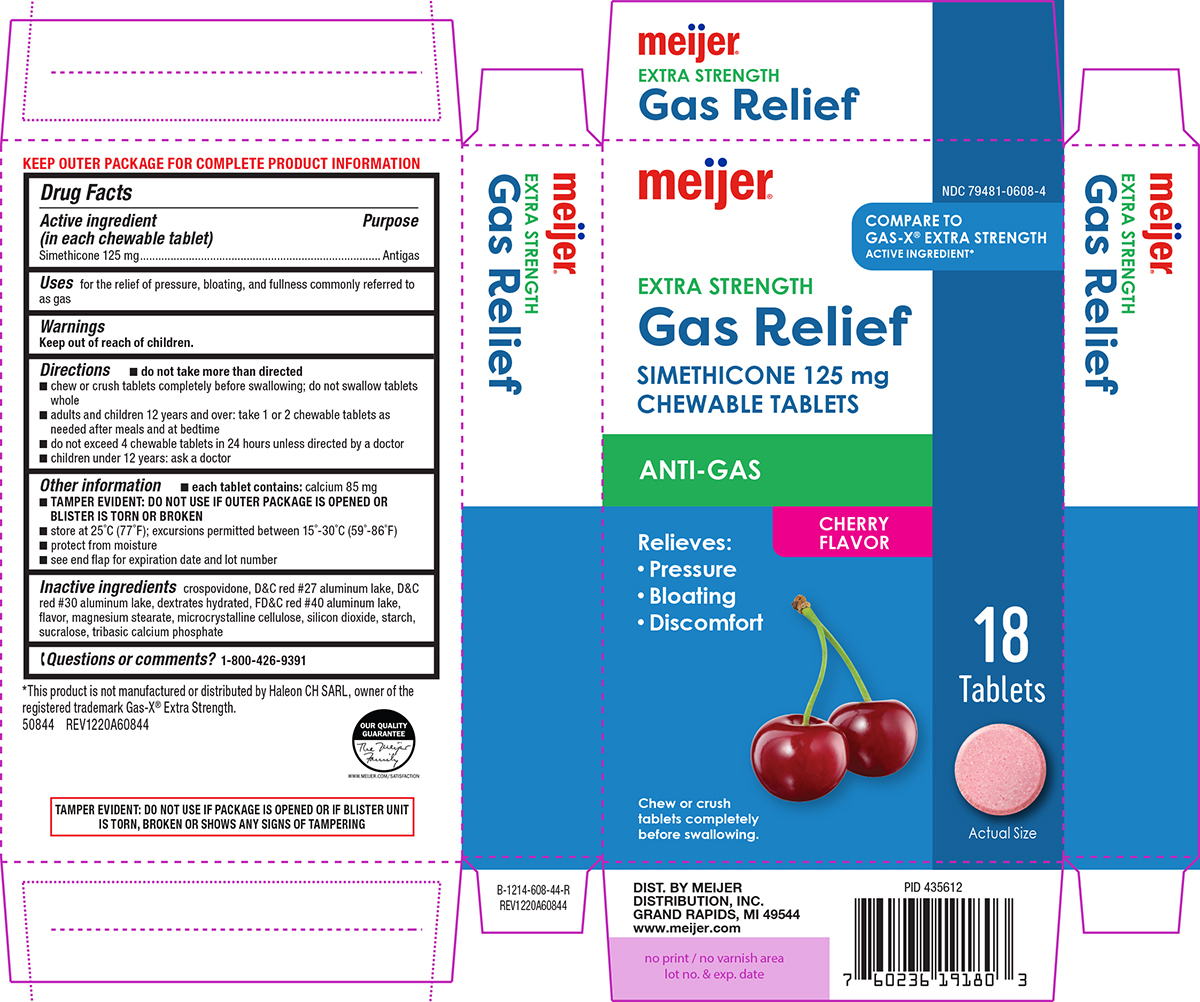 DRUG LABEL: Gas Relief
NDC: 79481-0608 | Form: TABLET, CHEWABLE
Manufacturer: Meijer Distribution, Inc.
Category: otc | Type: HUMAN OTC DRUG LABEL
Date: 20251115

ACTIVE INGREDIENTS: DIMETHICONE 125 mg/1 1
INACTIVE INGREDIENTS: CROSPOVIDONE, UNSPECIFIED; D&C RED NO. 27 ALUMINUM LAKE; D&C RED NO. 30 ALUMINUM LAKE; DEXTROSE MONOHYDRATE; FD&C RED NO. 40 ALUMINUM LAKE; MAGNESIUM STEARATE; MICROCRYSTALLINE CELLULOSE; SILICON DIOXIDE; STARCH, CORN; SUCRALOSE; TRIBASIC CALCIUM PHOSPHATE; DIMETHICONE 410

Meijer 44-608

Active ingredient (in each chewable tablet)

Simethicone 125 mg

Purpose

Antigas

Uses

for the relief of pressure, bloating, and fullness commonly referred to as gas

Directions

- do not take more than directed
- chew or crush tablets completely before swallowing; do not swallow tablets whole
- adults and children 12 years and over: take 1 or 2 chewable tablets as needed after meals and at bedtime
- do not exceed 4 chewable tablets in 24 hours unless directed by a doctor
- children under 12 years: ask a doctor

Other information

- each tablet contains: calcium 85 mg
- TAMPER EVIDENT: DO NOT USE IF OUTER PACKAGE IS OPENED OR BLISTER IS TORN OR BROKEN
- store at 25°C (77°F); excursions permitted between 15°-30°C (59°-86°F)
- protect from moisture
- see end flap for expiration date and lot number

Inactive ingredients

crospovidone, D&C red #27 aluminum lake, D&C red #30 aluminum lake, dextrates hydrated, FD&C red #40 aluminum lake, flavor, magnesium stearate, microcrystalline cellulose, silicon dioxide, starch, sucralose, tribasic calcium phosphate

Questions or comments?

1-800-426-9391

Principal display panel

NDC 79481-0608-4

Meijer®

COMPARE TO
GAS-X® EXTRA STRENGTH
ACTIVE INGREDIENT*

EXTRA STRENGTH
Gas Relief
SIMETHICONE 125 mg
CHEWABLE TABLETS

ANTI-GAS

Relieves:
● Pressure
● Bloating
● Discomfort

CHERRY
FLAVOR

18
Tablets

Actual Size

Chew or crush
tablets completely
before swallowing.

TAMPER EVIDENT: DO NOT USE IF PACKAGE IS OPENED OR IF BLISTER UNIT
IS TORN, BROKEN OR SHOWS ANY SIGNS OF TAMPERING

DIST. BY MEIJER
DISTRIBUTION, INC.
GRAND RAPIDS, MI 49544
www.meijer.com

*This product is not manufactured or distributed by Haleon CH SARL, owner of the
registered trademark Gas-X® Extra Strength.
50844 REV1220A60844

Meijer 44-608